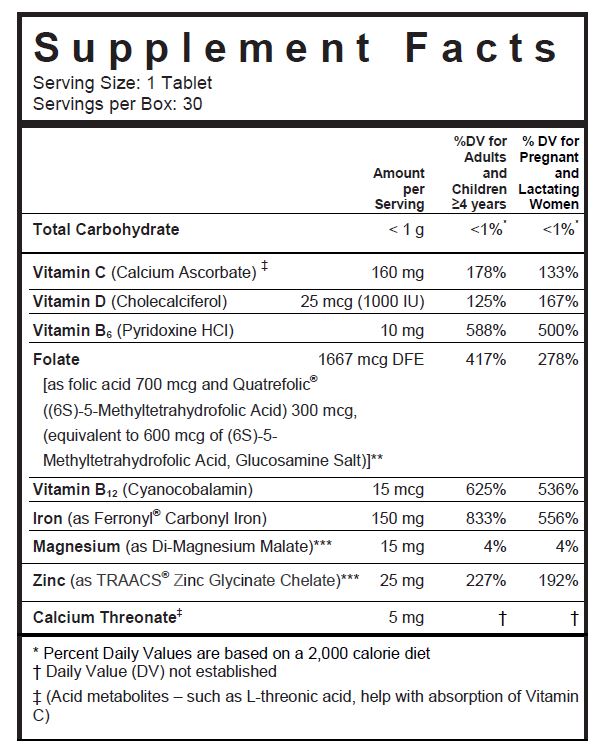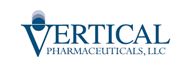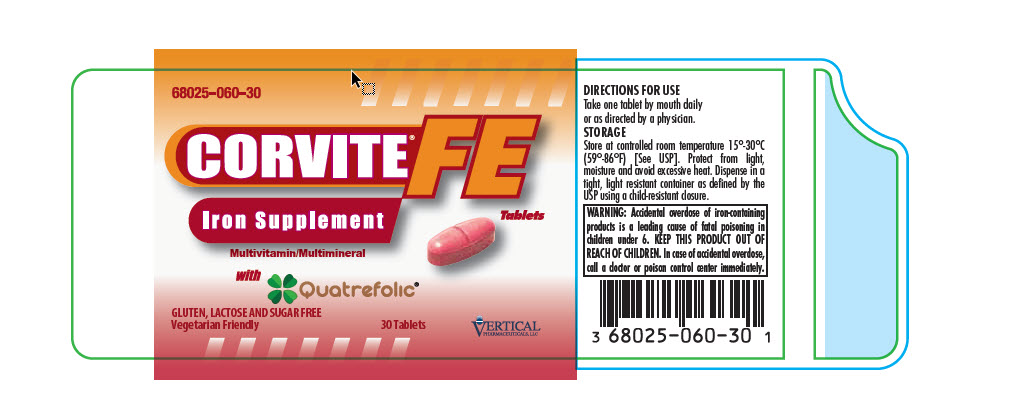 DRUG LABEL: Corvite FE
NDC: 68025-060 | Form: TABLET, COATED
Manufacturer: Vertical Pharmaceuticals, LLC
Category: other | Type: DIETARY SUPPLEMENT
Date: 20220107

ACTIVE INGREDIENTS: Calcium Ascorbate 160 mg/1 1; Calcium Threonate 5 mg/1 1; Cholecalciferol 1000 [iU]/1 1; Pyridoxine Hydrochloride 10 mg/1 1; Cyanocobalamin 15 ug/1 1; Magnesium Malate 15 mg/1 1; Zinc Glycinate 25 mg/1 1; FOLIC ACID 700 ug/1 1; 5-METHYLTETRAHYDROFOLIC ACID 300 ug/1 1; IRON PENTACARBONYL 150 mg/1 1
INACTIVE INGREDIENTS: Cellulose, Microcrystalline; Croscarmellose Sodium; POLYVINYL ALCOHOL, UNSPECIFIED; Magnesium Stearate; Silicon Dioxide; Hypromelloses; Titanium Dioxide; FD&C Red No. 40; Talc; FD&C YELLOW NO. 6; FD&C BLUE NO. 2; STARCH, CORN; ANHYDROUS DIBASIC CALCIUM PHOSPHATE; TRIACETIN

CORVITE® FE
Iron Supplement

SUPPLEMENT FACTS

Other Ingredients: Microcrystalline Cellulose, di-Calcium Phosphate, Pregelatinized Starch, Red Color Coating (Hydroxypropylmethyl Cellulose, Polyvinyl Alcohol, FD&C Red #40 Lake, Glycerol Triacetate, Titanium Dioxide, Talc, FD&C Yellow #6 Lake, FD&C Blue #2 Lake), Croscarmellose Sodium, Magnesium Stearate, Silicon Dioxide and Fumed Silica.

VEGETARIAN FRIENDLY

GLUTEN, LACTOSE AND SUGAR FREE

CORVITE® FE is a professionally prescribed hematinic multivitamin/multimineral dietary supplement used to improve the nutritional status of patients with iron deficiency; this includes women prior to conception, throughout pregnancy, and in the postnatal period for both lactating and non-lactating mothers.

HEALTH CLAIM

Other Ingredients: Microcrystalline Cellulose, DiCalcium Phosphate, Croscarmellose Sodium, Acacia, Isopropyl Alcohol, Povidone K30, Purified Water, Magnesium Stearate, TriPotassium Citrate, Citric Acid, Fumed Silica, Hypromellose, Ethyl Cellulose, Titanium Dioxide, Polyethylene Glycol, FD&C Red #40 Lake, Talc, Polysorbate 80, Hydroxypropyl Cellulose, Black Iron Oxide and Vegetable Oil.

CONTRAINDICATIONS

CORVITE®FE should not be used by patients with a known hypersensitivity to any of the listed ingredients. All iron compounds are contraindicated in patients with hemochromatosis, hemosiderosis, or hemolytic anemias.

WARNINGS

WARNING: Accidental overdose of iron-containing products is a leading cause of fatal poisoning in children under 6. KEEP THIS PRODUCT OUT OF REACH OF CHILDREN. In case of accidental overdose, call a doctor or poison control center immediately.

PRECAUTIONS

General: Do not exceed recommended dose. The type of anemia and the underlying cause or causes should be determined before starting therapy with CORVITE® FE. Since the anemia may be a result of a systemic disturbance, such as recurrent blood loss, the underlying cause or causes should be corrected, if possible.

Folic Acid: Folic acid alone is an improper therapy in the treatment of pernicious anemia and other megaloblastic anemias where vitamin B12 is deficient. Folic acid in doses above 0.1 mg daily may obscure pernicious anemia in that hematologic remission can occur while neurologic manifestations remain progressive. Allergic sensitization has been reported following both oral and parenteral administration of folic acid.

The patient’s medical conditions and consumption of other drugs, herbs, and/or supplements should be considered.

Pediatric Use: Safety and effectiveness in pediatric population have not been established.

Geriatric Use: Safety and effectiveness in elderly population have not been established.

DRUG INTERACTIONS

CORVITE® FE is not recommended for and should not be given to patients receiving levodopa because the action of levodopa is antagonized by pyridoxine. There is a possibility of increased bleeding due to pyridoxine interaction with anticoagulants (e.g., Aspirin, Heparin, Clopidogrel).

ADVERSE REACTIONS

Adverse reactions with iron therapy may include constipation, diarrhea, nausea, vomiting, dark stools and abdominal pain which are usually transient.

OVERDOSAGE

The clinical course of acute iron overdosage can be variable. Initial symptoms may include abdominal pain, nausea, vomiting, diarrhea, tarry stools, melena, hematemesis, hypotension, tachycardia, metabolic acidosis, hyperglycemia, dehydration, drowsiness, pallor, cyanosis, lassitude, seizures, shock and coma.

DESCRIPTION

CORVITE®FE is a red, oval shaped, bisected tablet imprinted with “VP060”.

DIRECTIONS FOR USE

Take one tablet by mouth daily or as directed by a physician.

HOW SUPPLIED

CORVITE®FE is available in bottles of 30 tablets.

Product Code: 68025-060-30

STORAGE

Store at controlled room temperature 15°-30°C (59°-86°F) [See USP]. Protect from light, moisture and avoid excessive heat. Dispense in a tight, light resistant container as defined by the USP using a child-resistant closure.

KEEP OUT OF REACH OF CHILDREN.

** Quatrefolic® is a registered trademark of Gnosis, SpA.
U.S. Patent No. 7,947,662.

***TRAACS® is a registered trademark of Albion International, Inc.
Malate covered by U.S. Patent No, 6,706,904;
Chelate covered by U.S. Patent No. 7,838,042.

Call your doctor about side effects. To report side effects, call Vertical Pharmaceuticals at 1-770-509-4500 or FDA at 1-800-FDA-1088 or www.fda.gov/medwatch.

PLR-CFE-00003-1 Rev. 12/2021

Distributed by:
Vertical Pharmaceuticals, LLC
Alpharetta, GA 30005
www.verticalpharma.com

PRINCIPAL DISPLAY PANEL - 30 Tablet Bottle Label

68025-060-30

CORVITE® FE
Iron Supplement
Tablets

Multivitamin/Multimineral

Gluten, Lactose, and Free
Vegetarian Friendly

30 Tablets

VERTICAL
PHARMACEUTICALS, LLC